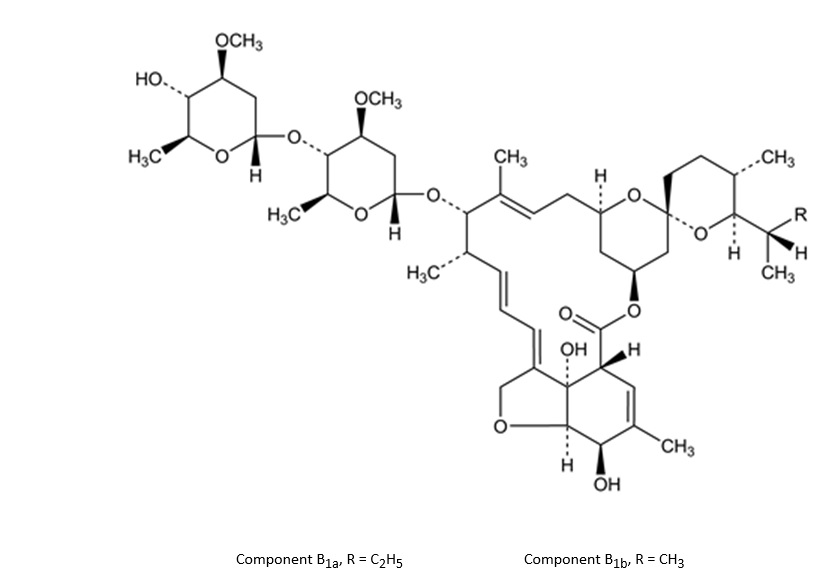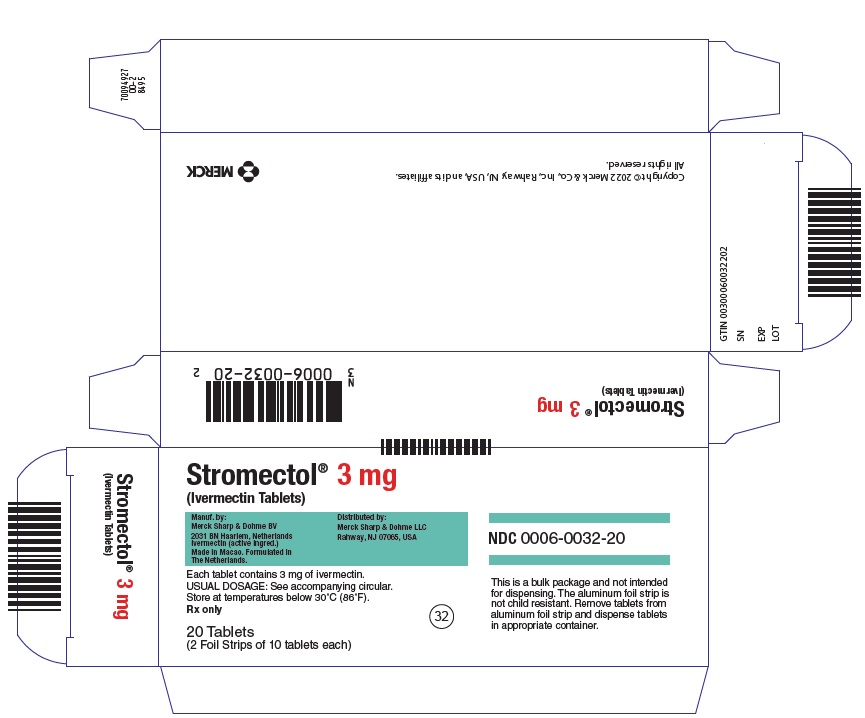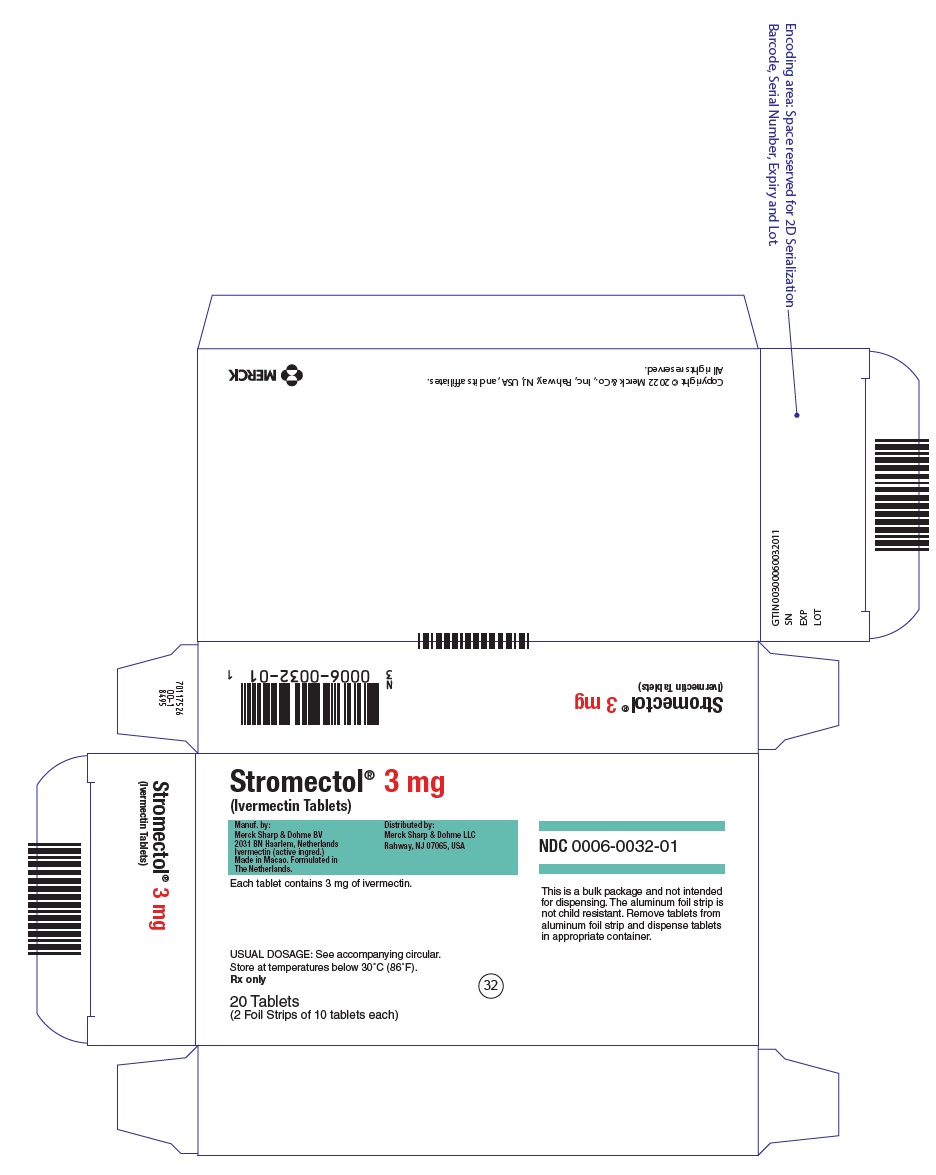 DRUG LABEL: STROMECTOL
NDC: 0006-0032 | Form: TABLET
Manufacturer: Merck Sharp & Dohme LLC
Category: prescription | Type: HUMAN PRESCRIPTION DRUG LABEL
Date: 20240920

ACTIVE INGREDIENTS: IVERMECTIN 3 mg/1 1
INACTIVE INGREDIENTS: MICROCRYSTALLINE CELLULOSE; STARCH, CORN; MAGNESIUM STEARATE; BUTYLATED HYDROXYANISOLE; ANHYDROUS CITRIC ACID

STROMECTOL®
(IVERMECTIN)
TABLETS

DESCRIPTION

STROMECTOL® (Ivermectin) is a semisynthetic, anthelmintic agent for oral administration. Ivermectin is derived from the avermectins, a class of highly active broad-spectrum, anti-parasitic agents isolated from the fermentation products of Streptomyces avermitilis. Ivermectin is a mixture containing at least 90% 5-O-demethyl-22,23-dihydroavermectin A1a and less than 10% 5-O-demethyl-25-de(1-methylpropyl)-22,23-dihydro-25-(1-methylethyl) avermectin A1a, generally referred to as 22,23-dihydroavermectin B1a and B1b, or H2B1a and H2B1b, respectively. The respective empirical formulas are C48H74O14 and C47H72O14, with molecular weights of 875.10 and 861.07, respectively. The structural formulas are:

Ivermectin is a white to yellowish-white, nonhygroscopic, crystalline powder with a melting point of about 155°C. It is insoluble in water but is freely soluble in methanol and soluble in 95% ethanol.

STROMECTOL is available in 3 mg tablets containing the following inactive ingredients: microcrystalline cellulose, pregelatinized starch, magnesium stearate, butylated hydroxyanisole, and citric acid powder (anhydrous).

CLINICAL PHARMACOLOGY

Pharmacokinetics

Following oral administration of ivermectin, plasma concentrations are approximately proportional to the dose. In two studies, after single 12 mg doses of STROMECTOL in fasting healthy volunteers (representing a mean dose of 165 mcg/kg), the mean peak plasma concentrations of the major component (H2B1a) were 46.6 (±21.9) (range: 16.4-101.1) and 30.6 (±15.6) (range: 13.9-68.4) ng/mL, respectively, at approximately 4 hours after dosing. Ivermectin is metabolized in the liver, and ivermectin and/or its metabolites are excreted almost exclusively in the feces over an estimated 12 days, with less than 1% of the administered dose excreted in the urine. The plasma half-life of ivermectin in man is approximately 18 hours following oral administration.

The safety and pharmacokinetic properties of ivermectin were further assessed in a multiple-dose clinical pharmacokinetic study involving healthy volunteers. Subjects received oral doses of 30 to 120 mg (333 to 2000 mcg/kg) ivermectin in a fasted state or 30 mg (333 to 600 mcg/kg) ivermectin following a standard high-fat (48.6 g of fat) meal. Administration of 30 mg ivermectin following a high-fat meal resulted in an approximate 2.5-fold increase in bioavailability relative to administration of 30 mg ivermectin in the fasted state.

In vitro studies using human liver microsomes and recombinant CYP450 enzymes have shown that ivermectin is primarily metabolized by CYP3A4. Depending on the in vitro method used, CYP2D6 and CYP2E1 were also shown to be involved in the metabolism of ivermectin but to a significantly lower extent compared to CYP3A4. The findings of in vitro studies using human liver microsomes suggest that clinically relevant concentrations of ivermectin do not significantly inhibit the metabolizing activities of CYP3A4, CYP2D6, CYP2C9, CYP1A2, and CYP2E1.

Microbiology

Ivermectin is a member of the avermectin class of broad-spectrum antiparasitic agents which have a unique mode of action. Compounds of the class bind selectively and with high affinity to glutamate-gated chloride ion channels which occur in invertebrate nerve and muscle cells. This leads to an increase in the permeability of the cell membrane to chloride ions with hyperpolarization of the nerve or muscle cell, resulting in paralysis and death of the parasite. Compounds of this class may also interact with other ligand-gated chloride channels, such as those gated by the neurotransmitter gamma-aminobutyric acid (GABA).

The selective activity of compounds of this class is attributable to the facts that some mammals do not have glutamate-gated chloride channels and that the avermectins have a low affinity for mammalian ligand-gated chloride channels. In addition, ivermectin does not readily cross the blood-brain barrier in humans.

Ivermectin is active against various life-cycle stages of many but not all nematodes. It is active against the tissue microfilariae of Onchocerca volvulus but not against the adult form. Its activity against Strongyloides stercoralis is limited to the intestinal stages.

Clinical Studies

Strongyloidiasis

Two controlled clinical studies using albendazole as the comparative agent were carried out in international sites where albendazole is approved for the treatment of strongyloidiasis of the gastrointestinal tract, and three controlled studies were carried out in the U.S. and internationally using thiabendazole as the comparative agent. Efficacy, as measured by cure rate, was defined as the absence of larvae in at least two follow-up stool examinations 3 to 4 weeks post-therapy. Based on this criterion, efficacy was significantly greater for STROMECTOL (a single dose of 170 to 200 mcg/kg) than for albendazole (200 mg b.i.d. for 3 days). STROMECTOL administered as a single dose of 200 mcg/kg for 1 day was as efficacious as thiabendazole administered at 25 mg/kg b.i.d. for 3 days.

Summary of Cure Rates for Ivermectin Versus Comparative Agents in the Treatment of Strongyloidiasis
 | Cure Rate [Number and % of evaluable patients] (%)
 | Ivermectin [170-200 mcg/kg] | Comparative Agent
Albendazole [200 mg b.i.d. for 3 days] Comparative International Study WHO Study | 24/26 (92) 126/152 (83) | 12/22 (55) 67/149 (45)
Thiabendazole [25 mg/kg b.i.d. for 3 days] Comparative International Study US Studies | 9/14 (64) 14/14 (100) | 13/15 (87) 16/17 (94)

In one study conducted in France, a non-endemic area where there was no possibility of reinfection, several patients were observed to have recrudescence of Strongyloides larvae in their stool as long as 106 days following ivermectin therapy. Therefore, at least three stool examinations should be conducted over the three months following treatment to ensure eradication. If recrudescence of larvae is observed, retreatment with ivermectin is indicated. Concentration techniques (such as using a Baermann apparatus) should be employed when performing these stool examinations, as the number of Strongyloides larvae per gram of feces may be very low.

Onchocerciasis

The evaluation of STROMECTOL in the treatment of onchocerciasis is based on the results of clinical studies involving 1278 patients. In a double-blind, placebo-controlled study involving adult patients with moderate to severe onchocercal infection, patients who received a single dose of 150 mcg/kg STROMECTOL experienced an 83.2% and 99.5% decrease in skin microfilariae count (geometric mean) 3 days and 3 months after the dose, respectively. A marked reduction of >90% was maintained for up to 12 months after the single dose. As with other microfilaricidal drugs, there was an increase in the microfilariae count in the anterior chamber of the eye at day 3 after treatment in some patients. However, at 3 and 6 months after the dose, a significantly greater percentage of patients treated with STROMECTOL had decreases in microfilariae count in the anterior chamber than patients treated with placebo.

In a separate open study involving pediatric patients ages 6 to 13 (n=103; weight range: 17-41 kg), similar decreases in skin microfilariae counts were observed for up to 12 months after dosing.

INDICATIONS AND USAGE

STROMECTOL is indicated for the treatment of the following infections:

Strongyloidiasis of the intestinal tract. STROMECTOL is indicated for the treatment of intestinal (i.e., nondisseminated) strongyloidiasis due to the nematode parasite Strongyloides stercoralis.

This indication is based on clinical studies of both comparative and open-label designs, in which 64-100% of infected patients were cured following a single 200-mcg/kg dose of ivermectin. (See CLINICAL PHARMACOLOGY, Clinical Studies.)

Onchocerciasis. STROMECTOL is indicated for the treatment of onchocerciasis due to the nematode parasite Onchocerca volvulus.

This indication is based on randomized, double-blind, placebo-controlled and comparative studies conducted in 1427 patients in onchocerciasis-endemic areas of West Africa. The comparative studies used diethylcarbamazine citrate (DEC-C).

NOTE: STROMECTOL has no activity against adult Onchocerca volvulus parasites. The adult parasites reside in subcutaneous nodules which are infrequently palpable. Surgical excision of these nodules (nodulectomy) may be considered in the management of patients with onchocerciasis, since this procedure will eliminate the microfilariae-producing adult parasites.

CONTRAINDICATIONS

STROMECTOL is contraindicated in patients who are hypersensitive to any component of this product.

WARNINGS

Historical data have shown that microfilaricidal drugs, such as diethylcarbamazine citrate (DEC-C), might cause cutaneous and/or systemic reactions of varying severity (the Mazzotti reaction) and ophthalmological reactions in patients with onchocerciasis. These reactions are probably due to allergic and inflammatory responses to the death of microfilariae. Patients treated with STROMECTOL for onchocerciasis may experience these reactions in addition to clinical adverse reactions possibly, probably, or definitely related to the drug itself. (See ADVERSE REACTIONS, Onchocerciasis.)

The treatment of severe Mazzotti reactions has not been subjected to controlled clinical trials. Oral hydration, recumbency, intravenous normal saline, and/or parenteral corticosteroids have been used to treat postural hypotension. Antihistamines and/or aspirin have been used for most mild to moderate cases.

Neurotoxicity with the use of ivermectin, including alteration of consciousness of variable severity (e.g., somnolence/drowsiness, stupor, and coma), confusion, disorientation and death, has been reported in patients without onchocerciasis or in patients with onchocerciasis in the absence of Loa loa infection. These reactions have generally resolved with supportive care and the discontinuation of ivermectin.

PRECAUTIONS

General

After treatment with microfilaricidal drugs, patients with hyperreactive onchodermatitis (sowda) may be more likely than others to experience severe adverse reactions, especially edema and aggravation of onchodermatitis.

Rarely, patients with onchocerciasis who are also heavily infected with Loa loa may develop a serious or even fatal encephalopathy either spontaneously or following treatment with an effective microfilaricide. In these patients, the following adverse experiences have also been reported: pain (including neck and back pain), red eye, conjunctival hemorrhage, dyspnea, urinary and/or fecal incontinence, difficulty in standing/walking, mental status changes, confusion, lethargy, stupor, seizures, or coma. This syndrome has been seen very rarely following the use of ivermectin. In individuals who warrant treatment with ivermectin for any reason and have had significant exposure to Loa loa-endemic areas of West or Central Africa, pretreatment assessment for loiasis and careful post-treatment follow-up should be implemented.

Information for Patients

STROMECTOL should be taken on an empty stomach with water. (See CLINICAL PHARMACOLOGY, Pharmacokinetics.)

Strongyloidiasis: The patient should be reminded of the need for repeated stool examinations to document clearance of infection with Strongyloides stercoralis.

Onchocerciasis: The patient should be reminded that treatment with STROMECTOL does not kill the adult Onchocerca parasites, and therefore repeated follow-up and retreatment is usually required.

Drug Interactions

Post-marketing reports of increased INR (International Normalized Ratio) have been rarely reported when ivermectin was co-administered with warfarin.

Carcinogenesis, Mutagenesis, Impairment of Fertility

Long-term studies in animals have not been performed to evaluate the carcinogenic potential of ivermectin.

Ivermectin was not genotoxic in vitro in the Ames microbial mutagenicity assay of Salmonella typhimurium strains TA1535, TA1537, TA98, and TA100 with and without rat liver enzyme activation, the Mouse Lymphoma Cell Line L5178Y (cytotoxicity and mutagenicity) assays, or the unscheduled DNA synthesis assay in human fibroblasts.

Ivermectin had no adverse effects on the fertility in rats in studies at repeated doses of up to 3 times the maximum recommended human dose of 200 mcg/kg (on a mg/m^2/day basis).

Pregnancy

Teratogenic Effects

Ivermectin has been shown to be teratogenic in mice, rats, and rabbits when given in repeated doses of 0.2, 8.1, and 4.5 times the maximum recommended human dose, respectively (on a mg/m^2/day basis). Teratogenicity was characterized in the three species tested by cleft palate; clubbed forepaws were additionally observed in rabbits. These developmental effects were found only at or near doses that were maternotoxic to the pregnant female. Therefore, ivermectin does not appear to be selectively fetotoxic to the developing fetus. There are, however, no adequate and well-controlled studies in pregnant women. Ivermectin should not be used during pregnancy since safety in pregnancy has not been established.

Nursing Mothers

STROMECTOL is excreted in human milk in low concentrations. Treatment of mothers who intend to breast-feed should only be undertaken when the risk of delayed treatment to the mother outweighs the possible risk to the newborn.

Pediatric Use

Safety and effectiveness in pediatric patients weighing less than 15 kg have not been established.

Geriatric Use

Clinical studies of STROMECTOL did not include sufficient numbers of subjects aged 65 and over to determine whether they respond differently from younger subjects. Other reported clinical experience has not identified differences in responses between the elderly and younger patients. In general, treatment of an elderly patient should be cautious, reflecting the greater frequency of decreased hepatic, renal, or cardiac function, and of concomitant disease or other drug therapy.

Strongyloidiasis in Immunocompromised Hosts

In immunocompromised (including HIV-infected) patients being treated for intestinal strongyloidiasis, repeated courses of therapy may be required. Adequate and well-controlled clinical studies have not been conducted in such patients to determine the optimal dosing regimen. Several treatments, i.e., at 2-week intervals, may be required, and cure may not be achievable. Control of extra-intestinal strongyloidiasis in these patients is difficult, and suppressive therapy, i.e., once per month, may be helpful.

ADVERSE REACTIONS

Strongyloidiasis

In four clinical studies involving a total of 109 patients given either one or two doses of 170 to 200 mcg/kg of STROMECTOL, the following adverse reactions were reported as possibly, probably, or definitely related to STROMECTOL:

Body as a Whole: asthenia/fatigue (0.9%), abdominal pain (0.9%)

Gastrointestinal: anorexia (0.9%), constipation (0.9%), diarrhea (1.8%), nausea (1.8%), vomiting (0.9%)

Nervous System/Psychiatric: dizziness (2.8%), somnolence (0.9%), vertigo (0.9%), tremor (0.9%)

Skin: pruritus (2.8%), rash (0.9%), and urticaria (0.9%).

In comparative trials, patients treated with STROMECTOL experienced more abdominal distention and chest discomfort than patients treated with albendazole. However, STROMECTOL was better tolerated than thiabendazole in comparative studies involving 37 patients treated with thiabendazole.

The Mazzotti-type and ophthalmologic reactions associated with the treatment of onchocerciasis or the disease itself would not be expected to occur in strongyloidiasis patients treated with STROMECTOL. (See ADVERSE REACTIONS, Onchocerciasis.)

Laboratory Test Findings

In clinical trials involving 109 patients given either one or two doses of 170 to 200 mcg/kg STROMECTOL, the following laboratory abnormalities were seen regardless of drug relationship: elevation in ALT and/or AST (2%), decrease in leukocyte count (3%). Leukopenia and anemia were seen in one patient.

Onchocerciasis

In clinical trials involving 963 adult patients treated with 100 to 200 mcg/kg STROMECTOL, worsening of the following Mazzotti reactions during the first 4 days post-treatment were reported: arthralgia/synovitis (9.3%), axillary lymph node enlargement and tenderness (11.0% and 4.4%, respectively), cervical lymph node enlargement and tenderness (5.3% and 1.2%, respectively), inguinal lymph node enlargement and tenderness (12.6% and 13.9%, respectively), other lymph node enlargement and tenderness (3.0% and 1.9%, respectively), pruritus (27.5%), skin involvement including edema, papular and pustular or frank urticarial rash (22.7%), and fever (22.6%). (See WARNINGS.)

In clinical trials, ophthalmological conditions were examined in 963 adult patients before treatment, at day 3, and months 3 and 6 after treatment with 100 to 200 mcg/kg STROMECTOL. Changes observed were primarily deterioration from baseline 3 days post-treatment. Most changes either returned to baseline condition or improved over baseline severity at the month 3 and 6 visits. The percentages of patients with worsening of the following conditions at day 3, month 3 and 6, respectively, were: limbitis: 5.5%, 4.8%, and 3.5% and punctate opacity: 1.8%, 1.8%, and 1.4%. The corresponding percentages for patients treated with placebo were: limbitis: 6.2%, 9.9%, and 9.4% and punctate opacity: 2.0%, 6.4%, and 7.2%. (See WARNINGS.)

In clinical trials involving 963 adult patients who received 100 to 200 mcg/kg STROMECTOL, the following clinical adverse reactions were reported as possibly, probably, or definitely related to the drug in ≥1% of the patients: facial edema (1.2%), peripheral edema (3.2%), orthostatic hypotension (1.1%), and tachycardia (3.5%). Drug-related headache and myalgia occurred in <1% of patients (0.2% and 0.4%, respectively). However, these were the most common adverse experiences reported overall during these trials regardless of causality (22.3% and 19.7%, respectively).

A similar safety profile was observed in an open study in pediatric patients ages 6 to 13.

The following ophthalmological side effects do occur due to the disease itself but have also been reported after treatment with STROMECTOL: abnormal sensation in the eyes, eyelid edema, anterior uveitis, conjunctivitis, limbitis, keratitis, and chorioretinitis or choroiditis. These have rarely been severe or associated with loss of vision and have generally resolved without corticosteroid treatment.

Laboratory Test Findings

In controlled clinical trials, the following laboratory adverse experiences were reported as possibly, probably, or definitely related to the drug in ≥1% of the patients: eosinophilia (3%) and hemoglobin increase (1%).

Post-Marketing Experience

The following adverse reactions have been reported since the drug was registered overseas:

Onchocerciasis

Conjunctival hemorrhage

All Indications

Hypotension (mainly orthostatic hypotension), worsening of bronchial asthma, toxic epidermal necrolysis, Stevens-Johnson syndrome, seizures, hepatitis, elevation of liver enzymes, and elevation of bilirubin.

Neurotoxicity including alteration of consciousness of variable severity (e.g., somnolence/drowsiness, stupor, and coma), confusion, disorientation, and death (see WARNINGS).

OVERDOSAGE

Cases of neurotoxicity, including alteration of consciousness of variable severity (e.g., somnolence/drowsiness, stupor, and coma), confusion, disorientation and death have been reported with recommended dosage and overdosage of ivermectin (see WARNINGS).

Significant lethality was observed in mice and rats after single oral doses of 25 to 50 mg/kg and 40 to 50 mg/kg, respectively. No significant lethality was observed in dogs after single oral doses of up to 10 mg/kg. At these doses, the treatment-related signs that were observed in these animals include ataxia, bradypnea, tremors, ptosis, decreased activity, emesis, and mydriasis.

In accidental intoxication with, or significant exposure to, unknown quantities of veterinary formulations of ivermectin in humans, either by ingestion, inhalation, injection, or exposure to body surfaces, the following adverse effects have been reported most frequently: rash, edema, headache, dizziness, asthenia, nausea, vomiting, and diarrhea. Other adverse effects that have been reported include: seizure, ataxia, dyspnea, abdominal pain, paresthesia, urticaria, and contact dermatitis.

In case of accidental poisoning, supportive therapy, if indicated, should include parenteral fluids and electrolytes, respiratory support (oxygen and mechanical ventilation if necessary) and pressor agents if clinically significant hypotension is present. Induction of emesis and/or gastric lavage as soon as possible, followed by purgatives and other routine anti-poison measures, may be indicated if needed to prevent absorption of ingested material.

DOSAGE AND ADMINISTRATION

Strongyloidiasis

The recommended dosage of STROMECTOL for the treatment of strongyloidiasis is a single oral dose designed to provide approximately 200 mcg of ivermectin per kg of body weight. See Table 1 for dosage guidelines. Patients should take tablets on an empty stomach with water. (See CLINICAL PHARMACOLOGY, Pharmacokinetics.) In general, additional doses are not necessary. However, follow-up stool examinations should be performed to verify eradication of infection. (See CLINICAL PHARMACOLOGY, Clinical Studies.)

Table 1: Dosage Guidelines for STROMECTOL for Strongyloidiasis
Body Weight (kg) | Single Oral Dose
 | Number of 3 mg Tablets
15-24 | 1 tablet
25-35 | 2 tablets
36-50 | 3 tablets
51-65 | 4 tablets
66-79 | 5 tablets
≥80 | 200 mcg/kg

Onchocerciasis

The recommended dosage of STROMECTOL for the treatment of onchocerciasis is a single oral dose designed to provide approximately 150 mcg of ivermectin per kg of body weight. See Table 2 for dosage guidelines. Patients should take tablets on an empty stomach with water. (See CLINICAL PHARMACOLOGY, Pharmacokinetics.) In mass distribution campaigns in international treatment programs, the most commonly used dose interval is 12 months. For the treatment of individual patients, retreatment may be considered at intervals as short as 3 months.

Table 2: Dosage Guidelines for STROMECTOL for Onchocerciasis
Body Weight (kg) | Single Oral Dose
 | Number of 3 mg Tablets
15-25 | 1 tablet
26-44 | 2 tablets
45-64 | 3 tablets
65-84 | 4 tablets
≥85 | 150 mcg/kg

HOW SUPPLIED

Tablets STROMECTOL 3 mg are white, round, flat, bevel-edged tablets coded MSD on one side and 32 on the other side. They are supplied as follows:

NDC 0006-0032-20 unit dose packages of 20.

NDC 0006-0032-01 unit dose packages of 20.

Storage

Store at temperatures below 30°C (86°F).

Dist. by: Merck Sharp & Dohme LLC
Rahway, NJ 07065, USA

For patent information: www.msd.com/research/patent

Copyright ©1996-2024 Merck & Co., Inc., Rahway, NJ, USA, and its affiliates.
All rights reserved.

Revised: 09/2024

uspi-mk0933-t-2409r023

This is a representative sample of the packaging. Please see How Supplied section for a complete list of available packaging. PRINCIPAL DISPLAY PANEL - 3 mg Tablet Blister Pack Carton

Stromectol® 3 mg
(Ivermectin Tablets)

Manuf. by:
Merck Sharp & Dohme BV
2031 BN Haarlem, Netherlands
Ivermectin (active ingred.)
Made in Macao. Formulated in
The Netherlands.

Distributed by:
Merck Sharp & Dohme LLC
Rahway, NJ 07065, USA

Each tablet contains 3 mg of ivermectin.
USUAL DOSAGE: See accompanying circular.
Store at temperatures below 30°C (86°F).
Rx only

20 Tablets
(2 Foil Strips of 10 tablets each)

32

NDC 0006-0032-20

This is a bulk package and not intended
for dispensing. The aluminum foil strip is
not child resistant. Remove tablets from
aluminum foil strip and dispense tablets
in appropriate container.

PRINCIPAL DISPLAY PANEL - 3 mg Tablet Blister Pack Carton

Stromectol® 3 mg
(Ivermectin Tablets)

Manuf. by:
Merck Sharp & Dohme BV
2031 BN Haarlem, Netherlands
Ivermectin (active ingred.)
Made in Macao. Formulated in
The Netherlands.

Distributed by:
Merck Sharp & Dohme LLC
Rahway, NJ 07065, USA

Each tablet contains 3 mg of ivermectin.

USUAL DOSAGE: See accompanying circular.
Store at temperatures below 30°C (86°F).
Rx only

20 Tablets
(2 Foil Strips of 10 tablets each)

32

NDC 0006-0032-01

This is a bulk package and not intended
for dispensing. The aluminum foil strip is
not child resistant. Remove tablets from
aluminum foil strip and dispense tablets
in appropriate container.